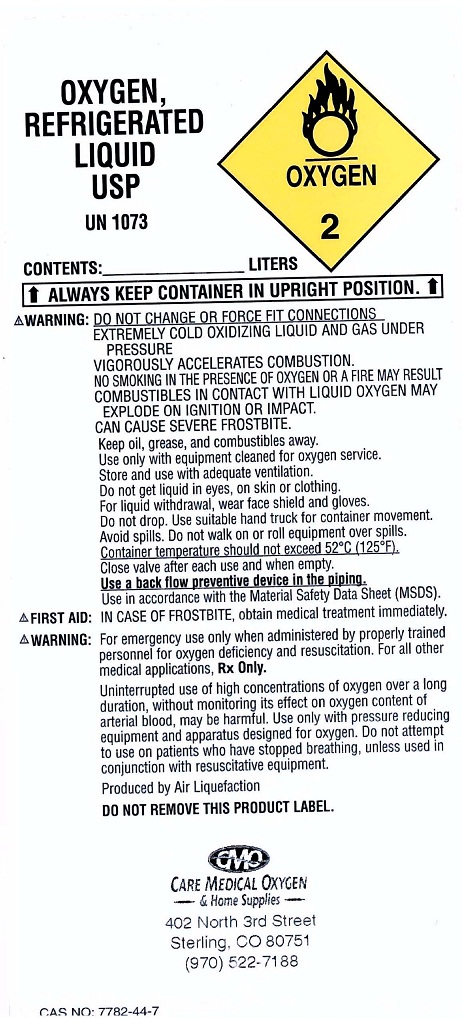 DRUG LABEL: Oxygen
NDC: 52193-001 | Form: GAS
Manufacturer: Care Medical Oxygen and Home Supplies
Category: prescription | Type: HUMAN PRESCRIPTION DRUG LABEL
Date: 20100412

ACTIVE INGREDIENTS: Oxygen 99 L/100 L

Oxygen